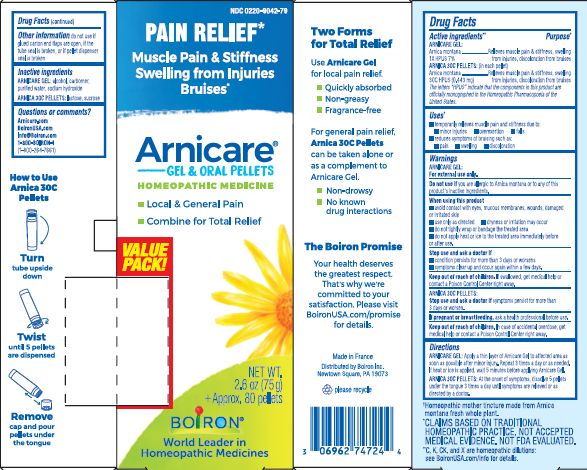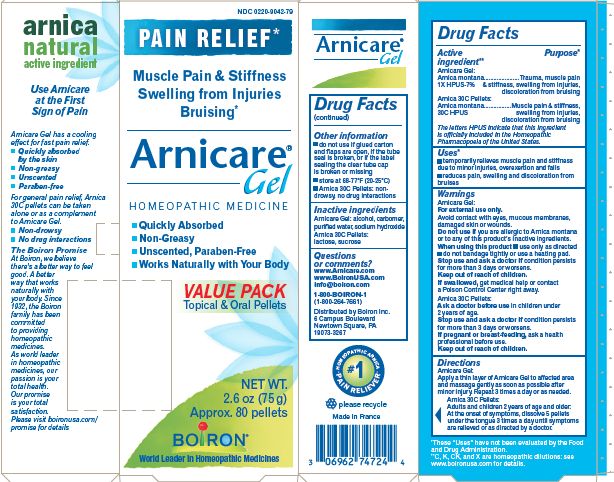 DRUG LABEL: Arnicare Value Pack
NDC: 0220-9042 | Form: KIT | Route: ORAL
Manufacturer: Laboratoires Boiron
Category: homeopathic | Type: HUMAN OTC DRUG LABEL
Date: 20231127

ACTIVE INGREDIENTS: ARNICA MONTANA 30 [hp_C]/1 1; ARNICA MONTANA 1 [hp_X]/1 g
INACTIVE INGREDIENTS: SUCROSE; LACTOSE; ALCOHOL; DIMETHICONE; WATER; SODIUM HYDROXIDE; CARBOMER HOMOPOLYMER TYPE C

Arnicare Gel Value Pack

Active ingredients**

Arnicare Gel: Arnica Montana 1X HPUS 7%

Arnica 30C pellets: (in each pellet) Arnica Montana 30C HPUS (0.443 mg)

The letters "HPUS" indicate that the components in this product are officially monographed in the Homeopathic Pharmacopoeia of the United States.

Uses*
temporarily relieves muscle pain and stiffness due to:

- minor injuries
- overexertion
- falls

reduces symptoms of bruising such as:

- pain
- swelling
- discoloration

Purpose*

Arnicare Gel: Arnica Montana 1X HPUS 7% ..... Relieves muscle pain & stiffness, swelling from injuries, discoloration from bruises
Arnica 30C Pellets: Arnica montana 30C HPUS .......... Relieves muscle pain & stiffness, swelling from injuries, discoloration from bruises

WARNINGS

Arnicare Gel: For external use only.

Do not use if you are allergic to Arnica montana or to any of this product's inactive ingredients.

When using this product

- avoid contact with eyes, mucous membranes, wounds, damaged or irritated skin
- use only as directed
- dryness or irritation may occur
- do not tightly wrap or bandage the treated area
- do not apply heat or ice to the treated area immediately before or after use.

Stop use and ask a doctor if

condition persists for more than 3 days or worsens
symptoms clear up and occur again within a few days.

ARNICA 30C PELLETS:

Stop use and ask a doctor if symptoms persist for more than 3 days or worsen.

PREGNANCY OR BREAST FEEDING

If pregnant or breastfeeding, ask a health professional before use.

Keep out of reach of children. If swallowed, get medical help or contact a Poison Control Center right away.

Directions

ARNICARE GEL: Apply a thin layer of Arnicare Gel to affected area as soon as possible after minor injury. Repeat 3 times a day or as needed. If heat or ice is applied, wait 5 minutes before applying Arnicare Gel.

ARNICA 30C PELLETS: At the onset of symptoms, dissolve 5 pellets under the tongue 3 times a day until symptoms are relieved or as directed by a doctor.

INACTIVE INGREDIENT

ARNICARE GEL: alcohol, carbomer, purified water, sodium hydroxide

ARNICA 30C PELLETS: lactose, sucrose.

QUESTIONS

Arnicare.com

BoironUSA.com

Info@Boiron.com

1-800-BOIRON-1

1-800-264-7661

do not use if glued carton end flaps are open, if the tube seal is broken, or if pellet dispenser seal is broken

Quickly absorbed, non-greasy, fragrance-free, non-drowsy, no known drug interactions

Pain Relief*

Muscle Pain & Stiffness Swelling from Injuries Bruises*

Local & General Pain

Combine for Total Relief

Gel: 1 tube 2.6 oz (75g)

Pellets: + approx. 80 pellets

How to dispense pellets? Turn tube upside down. Twist until 5 pellets are dispensed into cap. Carefully remove the cap and use it to pour pellets under the tongue.

*CLAIMS BASED ON TRADITIONAL HOMEOPATHIC PRACTICE NOT ACCEPTED MEDICAL EVIDENCE. NOT FDA EVALUATED.

**C,K,CK, and X are homeopathic dilutions: see BoironUSA.com/info for details.